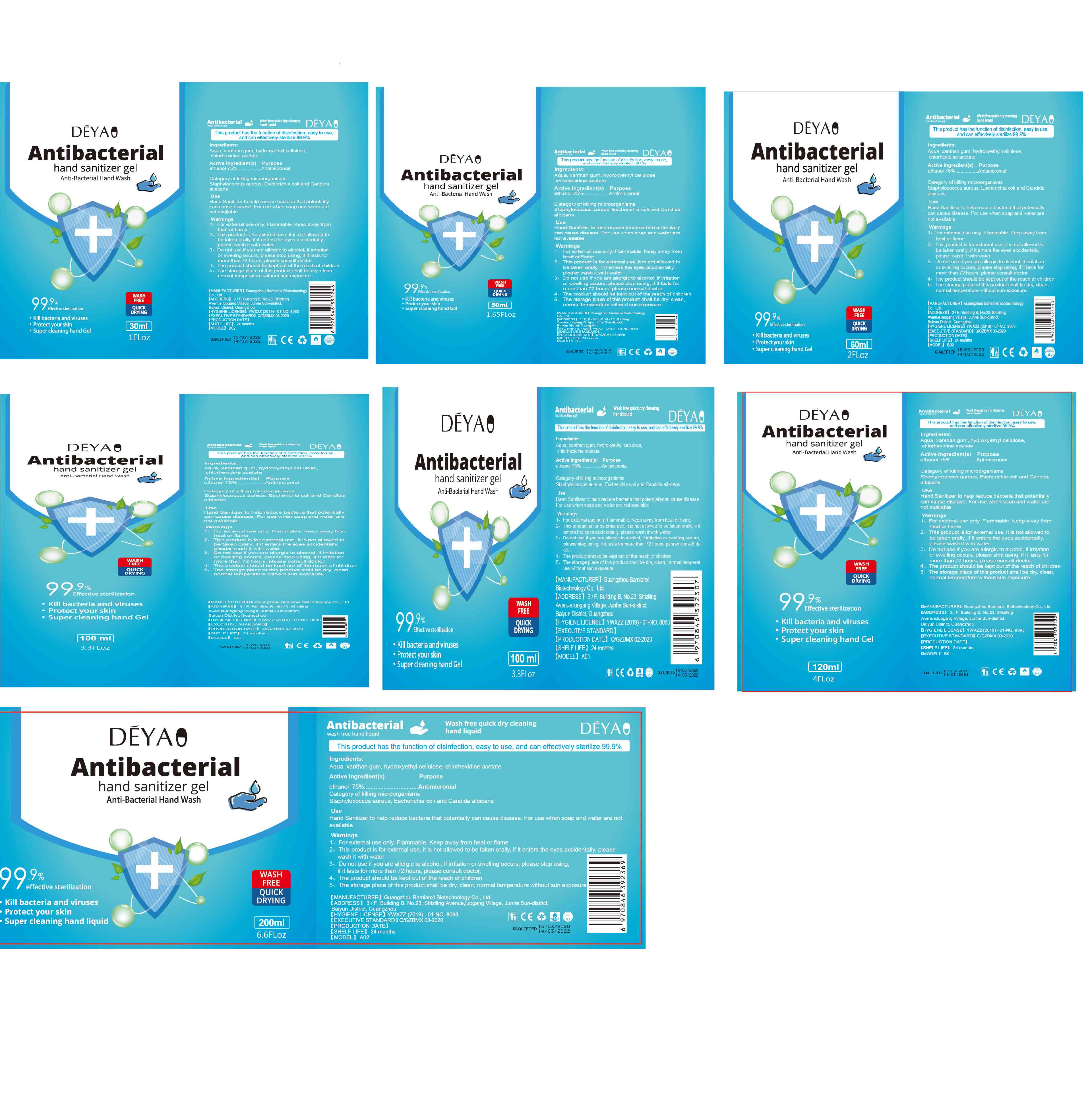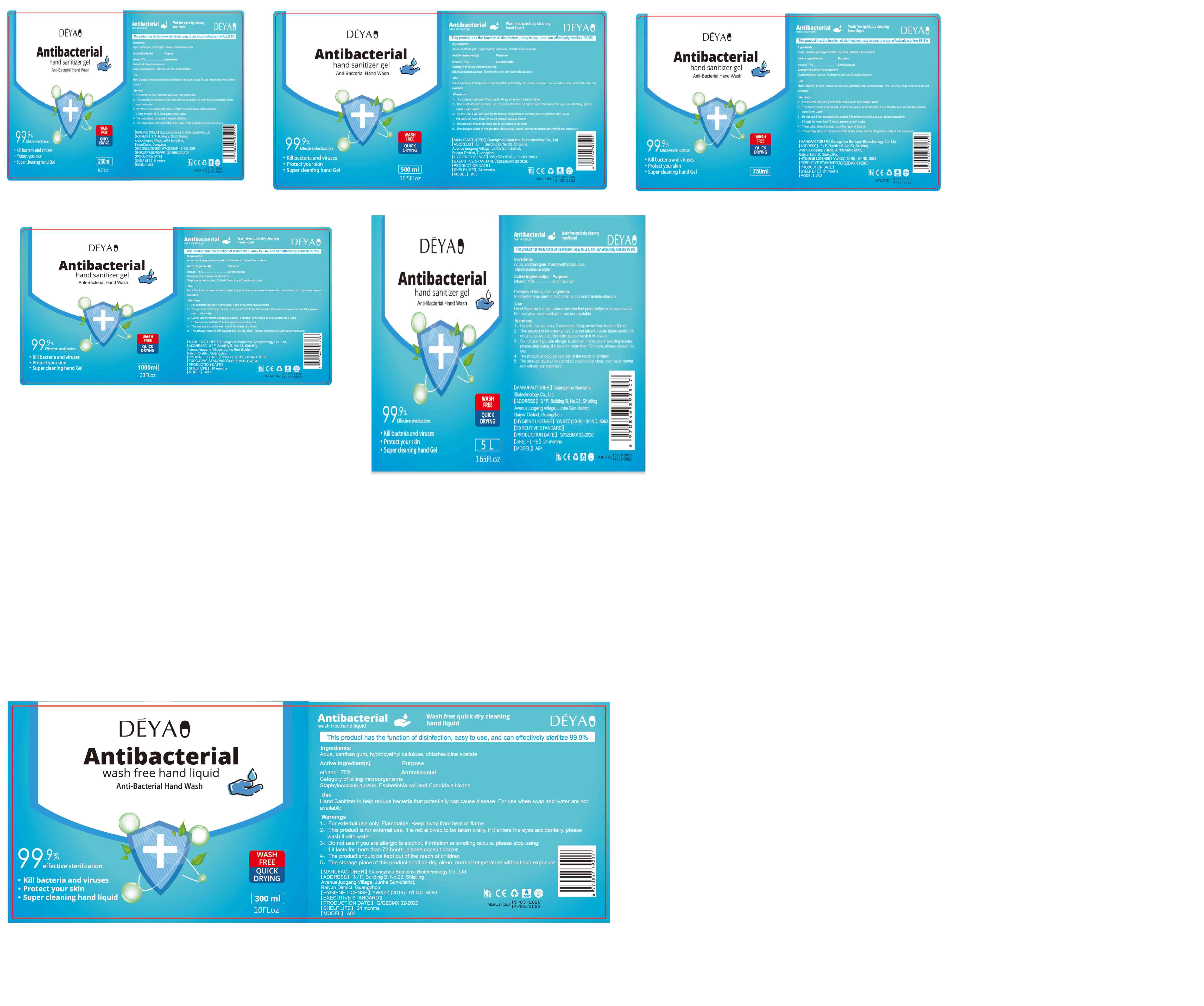 DRUG LABEL: Wash free quick dry cleaning hand gel
NDC: 78223-006 | Form: GEL
Manufacturer: Guangzhou Bamianxi Biotechnology Co., Ltd
Category: otc | Type: HUMAN OTC DRUG LABEL
Date: 20200605

ACTIVE INGREDIENTS: ALCOHOL 75 mL/100 mL
INACTIVE INGREDIENTS: CHLORHEXIDINE ACETATE; XANTHAN GUM; HYDROXYETHYL CELLULOSE (2000 CPS AT 1%); WATER

Active Ingredient(s)

Ethanol 75% v/v. Purpose: Antiseptic

Purpose

Antimicronial

Use

Hand Sanitizer to help reduce bacteria that potentially can cause disease. For use when soap and water arenot available

Warnings

1. For external use only. Flammable. Keep away fromheat or flame

2. This product is for external use, it is not allowed tobe taken orally, if it enters the eyes accidentallyplease wash it with water

3. Do not use if you are allergic to alcohol, if imitationor swelling occurs, please stop using, if it lasts formore than 72 hours, please consult doctor.

4. The product should be kept out of the reach of children5. The storage place of this product shall be dry, cleannormal temperature without sun exposure

Do not use

- /

WHEN USING

2. This product is for external use, it is not allowed tobe taken orally, if it enters the eyes accidentallyplease wash it with water

STOP USE

/

KEEP OUT OF REACH OF CHILDREN

The product should be kept out of the reach of children

Directions

- Hand Sanitizer to help reduce bacteria that potentiallycan cause disease. For use when soap and water arenot available

Other information

- The storage place of this product shall be dry, clean normal temperature without sun exposure

Inactive ingredients

Aqua, xanthan gum, hydroxyethyl cellulosechlorhexidine acetate